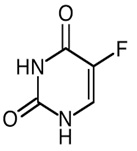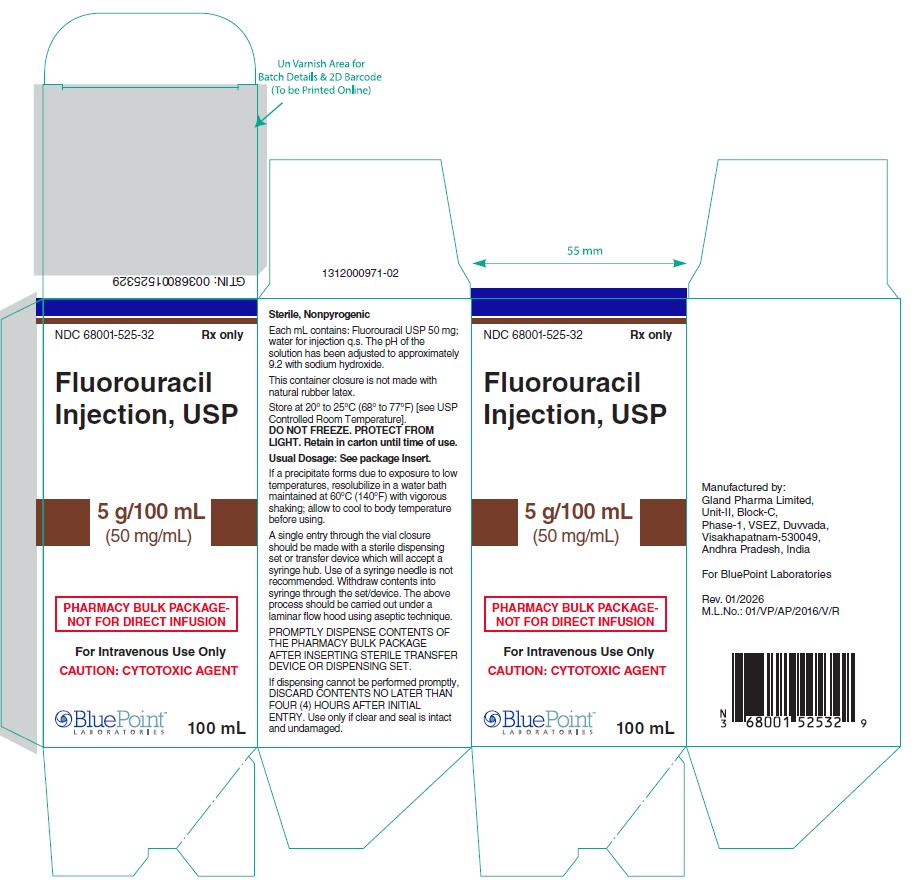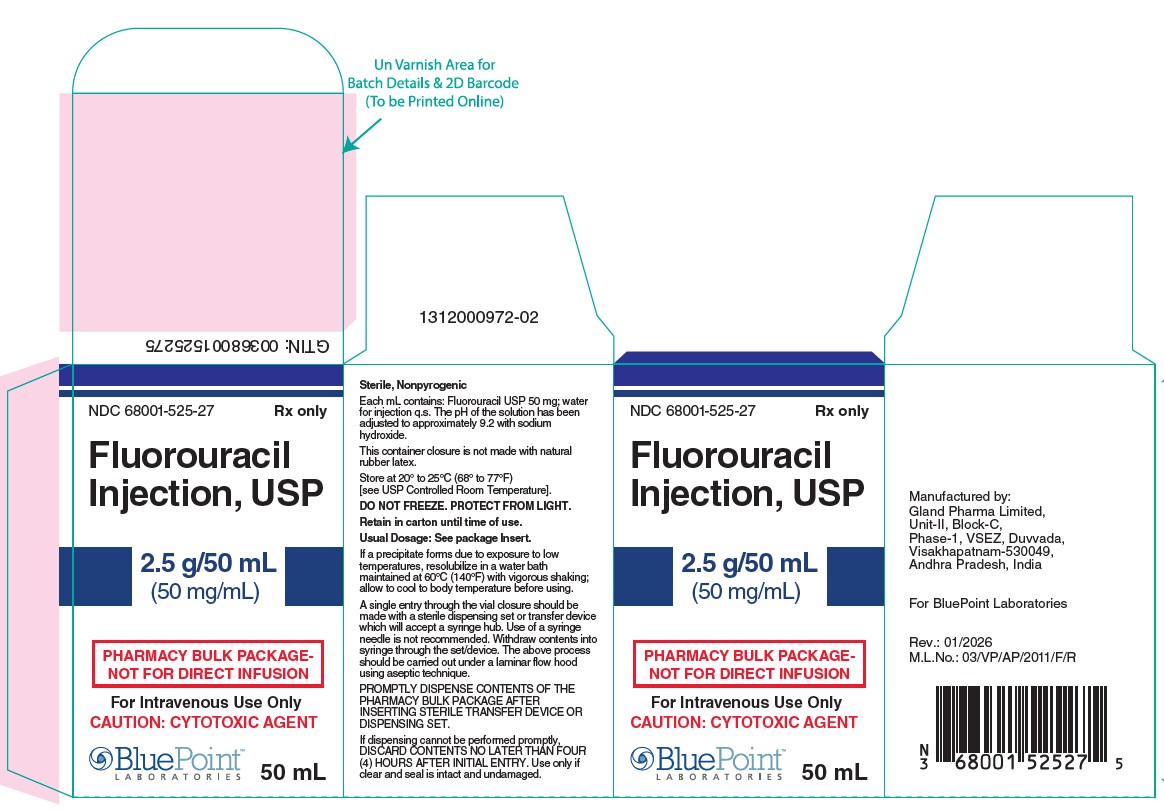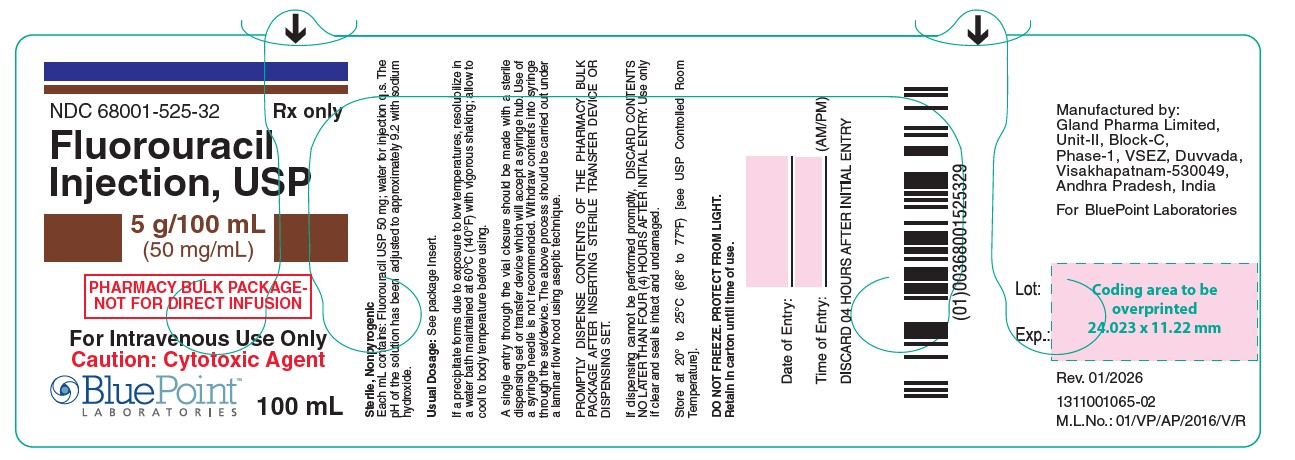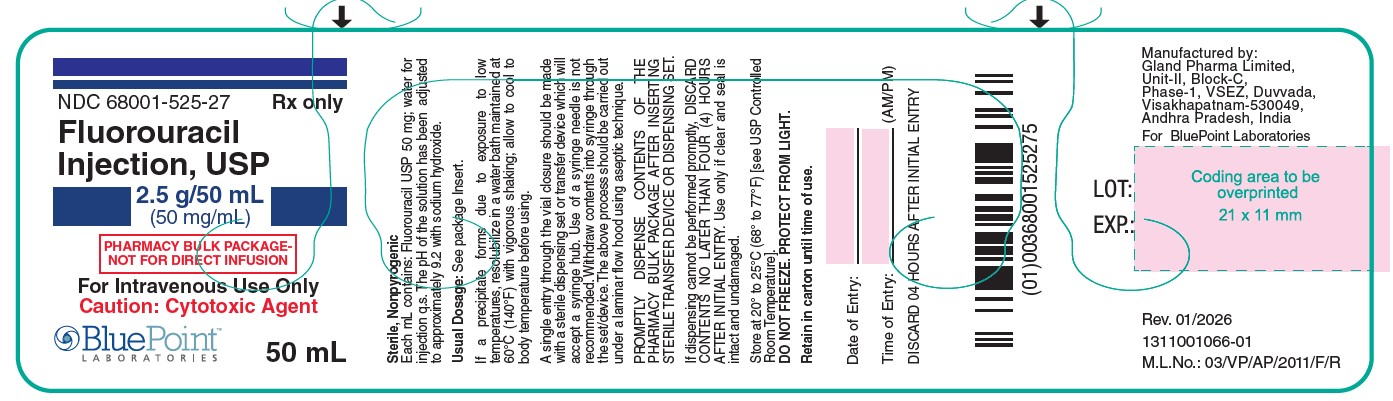 DRUG LABEL: Fluorouracil
NDC: 68001-525 | Form: INJECTION, SOLUTION
Manufacturer: BluePoint Laboratories
Category: prescription | Type: HUMAN PRESCRIPTION DRUG LABEL
Date: 20260226

ACTIVE INGREDIENTS: FLUOROURACIL 50 mg/1 mL
INACTIVE INGREDIENTS: SODIUM HYDROXIDE

HIGHLIGHTS OF PRESCRIBING INFORMATION

These highlights do not include all the information needed to use FLUOROURACIL INJECTION safely and effectively. See full prescribing information for FLUOROURACIL INJECTION.
FLUOROURACIL injection, for intravenous use
Initial U.S. Approval: 1962

WARNING: SERIOUS ADVERSE REACTIONS OR DEATH IN PATIENTS WITH COMPLETE DPD DEFICIENCY

See full prescribing information for complete boxed warning.

Serious adverse reactions or death may occur in patients with complete DPD deficiency. Test patients for genetic

variants of DPYD prior to initiating fluorouracil unless immediate treatment is necessary. Avoid use of fluorouracil in patients with certain homozygous or compound heterozygous DPYD variants that result in complete DPD deficiency. (2.1, 5.1)

RECENT MAJOR CHANGES

Boxed Warning 10/2025

Dosage and Administration (2.1) 10/2025

Warnings and Precautions, Serious Adverse Reactions or Death

from Dihydropyrimidine Dehydrogenase (DPD) Deficiency (5.1) 10/2025

1 INDICATIONS & USAGE

Fluorouracil is a nucleoside metabolic inhibitor indicated for the treatment of patients with

• Adenocarcinoma of the Colon and Rectum (1.1)
• Adenocarcinoma of the Breast (1.2)
• Gastric Adenocarcinoma (1.3)
• Pancreatic Adenocarcinoma (1.4)

2 DOSAGE & ADMINISTRATION

• Fluorouracil is recommended for administration either as an intravenous bolus or as an intravenous infusion. (2.2)
• See Full Prescribing Information for dose individualization (2.2) and dose modifications due to adverse reactions (2.7)
• See Full Prescribing Information for recommended doses of fluorouracil for adenocarcinoma of the colon and rectum (2.3) and for recommended doses of fluorouracil as a component of a chemotherapy regimen for adenocarcinoma of the breast (2.4), gastric adenocarcinoma (2.5), pancreatic adenocarcinoma (2.6)
• Pharmacy Bulk Package: Prepare doses for more than one patient in a Pharmacy Admixture Service under appropriate conditions for cytotoxic drugs. Do not inject entire contents of vial directly into patients. Use within 4 hours of puncture (2.8, 2.9)

3 DOSAGE FORMS & STRENGTHS

Injection: 2.5 g in a 50 mL vial in a pharmacy bulk package (3)
5 g in a 100 mL vial in a pharmacy bulk package (3)

4 CONTRAINDICATIONS

None (4)

5 WARNINGS AND PRECAUTIONS

• Cardiotoxicity:Fluorouracil can cause cardiotoxicity, including angina, myocardial infarction/ischemia, arrhythmia, and heart failure. Withhold fluorouracil for cardiac toxicity. (5.2)
• Hyperammonemic Encephalopathy:Altered mental status, confusion, disorientation, coma, or ataxia with elevated serum ammonia level can occur within 72 hours of initiation of fluorouracil. Withhold fluorouracil and initiate ammonia-lowering therapy. (5.3)
• Neurologic Toxicity:Fluorouracil can cause acute cerebellar syndrome, confusion, disorientation, ataxia, or visual disturbances. Withhold fluorouracil for neurologic toxicity. (5.4)
• Diarrhea:Fluorouracil can cause severe diarrhea. Withhold fluorouracil for severe diarrhea until resolved. (5.5)
• Palmar-Plantar Erythrodysesthesia (Hand-Foot Syndrome):Fluorouracil can cause hand-foot syndrome. If severe, discontinue fluorouracil until resolved or decreased to Grade 1, then resume at a reduced dose. (5.6)
• Myelosuppression:Fluorouracil can cause severe and fatal myelosuppression. Withhold fluorouracil until severe myelosuppression resolves, then resume at a reduced dose. (5.7)
• Mucositis:Fluorouracil can cause severe mucositis. Discontinue fluorouracil until resolved or decreased to Grade 1, then resume at a reduced dose. (5.8)
• Increased Risk of Elevated INR with Warfarin:Concurrent administration with warfarin can result in clinically significant increases in coagulation parameters: Closely monitor INR and prothrombin time. (5.9)
• Embryofetal Toxicity:Fluorouracil can cause fetal harm. Advise females and males of reproductive potential of the potential risk to a fetus. (5.10, 8.1, 8.6)

6 ADVERSE REACTIONS

To report SUSPECTED ADVERSE REACTIONS, contact BluePoint Laboratories at 1-800-707-4621 or FDA at 1-800-FDA-1088 or www.fda.gov/medwatch

7 DRUG INTERACTIONS

[Enter highlight text here]

8 USE IN SPECIFIC POPULATIONS

• Nursing Mothers: Discontinue drug or discontinue nursing. (8.3)
• Females and Males of Reproductive Potential: Provide pregnancy planning and prevention counseling. (5.10, 8.1, 8.6)

FULL PRESCRIBING INFORMATION

WARNING: SERIOUS ADVERSE REACTIONS OR DEATH IN PATIENTS WITH COMPLETE DPD DEFICIENCY

Increased Risk of Serious Adverse Reactions or Death in Patients with Complete DPD Deficiency

Test patients for genetic variants of DPYD prior to initiating fluorouracil unless immediate treatment is necessary.

Avoid use of fluorouracil in patients with certain homozygous or compound heterozygous DPYD variants that result in

complete DPD deficiency [see Warnings and Precautions (5.1)].

1 INDICATIONS & USAGE

Fluorouracil is indicated for the treatment of patients with:

2 DOSAGE & ADMINISTRATION

2.1 Evaluation and Testing for DPD Deficiency Before Initiating fluorouracil

Prior to initiating fluorouracil, test patients for genetic variants of the DPYD gene unless immediate treatment is necessary. An FDA authorized test for the detection of the DPYD gene to identify patients at risk of serious adverse reactions with fluorouracil is not currently available. Currently available tests used to identify DPYD variants may vary in accuracy and design (e.g., which DPYD variant(s) they identify).

Avoid use of fluorouracil in patients known to have certain homozygous or compound heterozygous DPYD variants that result in complete DPD deficiency. No fluorouracil dose has been proven safe for patients with complete DPD deficiency. For patients with partial DPD deficiency, individualize the dosage and modify based on tolerability and intent of treatment [see Warnings and Precautions (5.1)].

2.2 General Dosage Information

Fluorouracil is recommended for administration either as an intravenous bolus or as anintravenous infusion. Do not inject the entire contents of the vial directly into patients. Individualize the dose and dosing schedule of fluorouracil based on tumor type, the specific regimen administered, disease state, response to treatment, and patient risk factors.

2.3 Recommended Dosage for Adenocarcinoma of the Colon and Rectum

- The recommended dose of fluorouracil, administered in an infusional regimen in combination with leucovorin alone, or in combination with leucovorin and oxaliplatin or irinotecan, is 400 mg/m2 by intravenous bolus on Day 1, followed by 2400 mg/m2 to 3000 mg/m2 intravenously as a continuous infusion over 46 hours every two weeks.
- The recommended dose of fluorouracil, if administered in a bolus dosing regimen in combination with leucovorin, is 500 mg/m2 by intravenous bolus on Days 1, 8, 15, 22, 29, and 36 in 8-week cycles.

2.4 Recommended Dosage for Adenocarcinoma of the Breast

• The recommended dose of fluorouracil, administered as a component of a cyclophosphamide based multidrug regimen, is 500 mg/m2 or 600 mg/m2 intravenously on Days 1 and 8 every 28 days for 6 cycles.

2.5 Recommended Dosage for Gastric Adenocarcinoma

- The recommended dose of fluorouracil, administered as a component of a platinum-containing multidrug chemotherapy regimen, is 200 mg/m2 to 1000 mg/m2 intravenously as a continuous infusion over 24 hours. The frequency of dosing in each cycle and the length of each cycle will depend on the dose of fluorouracil and the specific regimen administered.

2.6 Recommended Dosage for Pancreatic Adenocarcinoma

- The recommended dose of fluorouracil, administered as an infusional regimen in combination with leucovorin or as a component of a multidrug chemotherapy regimen that includes leucovorin, is 400 mg/m2 intravenous bolus on Day 1, followed by 2400 mg/m2 intravenously as a continuous infusion over 46 hours every two weeks.

2.7 Dose Modifications

Withhold fluorouracil for any of the following:

• Development of angina, myocardial infarction/ischemia, arrhythmia, or heart failure in patients with no history of coronary artery disease or myocardial dysfunction [see Warnings and Precautions (5.2)]

• Hyperammonemic encephalopathy [see Warnings and Precautions (5.3)]

• Acute cerebellar syndrome, confusion, disorientation, ataxia, or visual disturbances [see Warnings and Precautions (5.4)]

• Grade 3 or 4 diarrhea [see Warnings and Precautions (5.5)]

• Grade 2 or 3 palmar-plantar erythrodysesthesia (hand-foot syndrome) [see Warnings and Precautions (5.6)]

• Grade 3 or 4 mucositis [see Warnings and Precautions (5.8)]

• Grade 4 myelosuppression [see Warnings and Precautions (5.7)]

Upon resolution or improvement to Grade 1 diarrhea, mucositis, myelosuppression, or palmarplantar erythrodysesthesia, resume fluorouracil administration at a reduced dose.

There is no recommended dose for resumption of fluorouracil administration following development of any of the following adverse reactions:

• Cardiac toxicity

• Hyperammonemic encephalopathy

• Acute cerebellar syndrome, confusion, disorientation, ataxia, or visual disturbances

2.8 Preparation for Administration

Fluorouracil is supplied in a pharmacy bulk package consisting of a vial. The pharmacy bulk package can be used to prepare doses for more than one patient. It is not supplied with a sterile transfer device, which is required for dispensing when multiple doses will be prepared from the single vial. The 50 mL/100 mL vial is only intended for preparation in a Pharmacy Admixture Service under appropriate conditions for cytotoxic drugs [see References (15)]. Store vial at room temperature.

Using aseptic conditions, penetrate the container closure once with a suitable sterile transfer device or dispensing set that allows measured distribution of the contents. Record the date and time the vial was opened on the vial label. Discard the pharmacy bulk package 4 hours after penetration of the container closure.

Withdraw the calculated dose for an individual patient into a sterile syringe. Inspect the solution in syringe for particulate matter and discoloration prior to administration or further dilution. Discard syringe if the solution is discolored or contains particulate matter.

2.9 Administration

Do not administer in the same intravenous line concomitantly with other medicinal products. For bolus administration, store undiluted fluorouracil in the syringe for up to 4 hours at room temperature (25°C). Administer fluorouracil as an intravenous bolus through an established intravenous line.

Store diluted solutions of fluorouracil for up to 4 hours at room temperature (25°C) prior to administration to the patient. For intravenous infusion regimens, administer through a central venous line using an infusion pump.

3 DOSAGE FORMS & STRENGTHS

Fluorouracil injection USP is supplied as a pharmacy bulk package as a vial containing
2.5 g/50 mL (50 mg/mL) and 5 g/100 mL (50 mg/mL) fluorouracil.

4 CONTRAINDICATIONS

None.

5 WARNINGS AND PRECAUTIONS

5.1 Serious Adverse Reactions or Death from Dihydropyrimidine Dehydrogenase (DPD) Deficiency

Patients with certain homozygous or compound heterozygous variants in the DPYDgene known to result in complete or near complete absence of DPD activity (complete DPD deficiency) are at increased risk for acute early-onset toxicity and serious, including fatal, adverse reactions due to fluorouracil (e.g., mucositis, diarrhea, neutropenia, and neurotoxicity). Patients with partial DPD activity (partial DPD deficiency) may also have increased risk of serious, or fatal, adverse reactions.

Prior to initiating fluorouracil, test patients for genetic variants of the DPYD gene unless immediate treatment is necessary [see Clinical Pharmacology (12.5)]. Serious adverse reactions may still occur even if no DPYD variants are identified.

Avoid use of fluorouracil in patients with certain homozygous or compound heterozygous DPYD variants that result in complete DPD deficiency.

Withhold or permanently discontinue fluorouracil based on clinical assessment of the onset, duration, and severity of adverse reactions in patients with evidence of acute early-onset or unusually severe reactions. No fluorouracil dose has been proven safe for patients with complete DPD deficiency. For patients with partial DPD deficiency, individualize the dosage and modify based on tolerability and intent of treatment.

An FDA-authorized test for the detection of genetic variants of the DPYD gene to identify patients at risk of serious adverse reactions with fluorouracil treatment is not currently available. Currently available tests used to identify DPYD variants may vary in accuracy and design (e.g., which DPYD variant(s) they identify).

5.2 Cardiotoxicity

Fluorouracil can cause cardiotoxicity, including angina, myocardial infarction/ischemia, arrhythmia, and heart failure, based on postmarketing reports. Reported risk factors for cardiotoxicity are administration by continuous infusion rather than intravenous bolus and presence of coronary artery disease. Withhold fluorouracil for cardiotoxicity. The risks of resumption of fluorouracil in patients with cardiotoxicity that has resolved have not been established.

5.3 Hyperammonemic Encephalopathy

Fluorouracil can cause hyperammonemic encephalopathy in the absence of liver disease or other identifiable cause, based on postmarketing reports. Signs or symptoms of hyperammonemic encephalopathy began within 72 hours after initiation of fluorouracil infusion; these included altered mental status, confusion, disorientation, coma, or ataxia, in the presence of concomitant elevated serum ammonia level. Withhold fluorouracil for hyperammonemic encephalopathy and initiate ammonia-lowering therapy. The risks of resumption of fluorouracil in patients with hyperammonemic encephalopathy that has resolved have not been established

5.4 Neurologic Toxicity

Fluorouracil can cause neurologic toxicity, including acute cerebellar syndrome and other neurologic events, based on postmarketing reports. Neurologic symptoms included confusion, disorientation, ataxia, or visual disturbances. Withhold fluorouracil for neurologic toxicity. There are insufficient data on the risks of resumption of fluorouracil in patients with neurologic toxicity that has resolved.

5.5 Diarrhea

Fluorouracil can cause severe diarrhea. Withhold fluorouracil for Grade 3 or 4 diarrhea until resolved or decreased in intensity to Grade 1, then resume fluorouracil at a reduced dose. Administer fluids, electrolyte replacement, or antidiarrheal treatments as necessary.

5.6 Palmar-Plantar Erythrodysesthesia (Hand-Foot Syndrome)

Fluorouracil can cause palmar-plantar erythrodysesthesia, also known as hand-foot syndrome (HFS). Symptoms of HFS include a tingling sensation, pain, swelling, and erythema with tenderness, and desquamation. HFS occurs more commonly when fluorouracil is administered as a continuous infusion than when fluorouracil is administered as a bolus injection, and has been reported to occur more frequently in patients with previous exposure to chemotherapy. HFS is generally observed after 8-9 weeks of fluorouracil administration but may occur earlier. Institute supportive measures for symptomatic relief of HFS. Withhold fluorouracil administration for Grade 2 or 3 HFS; resume fluorouracil at a reduced dose when HFS is completely resolved or decreased in severity to Grade 1.

5.7 Myelosuppression

Fluorouracil can cause severe and fatal myelosuppression which may include neutropenia, thrombocytopenia, and anemia. The nadir in neutrophil counts commonly occurs between 9 and 14 days after fluorouracil administration. Obtain complete blood counts prior to each treatment cycle, weekly if administered on a weekly or similar schedule, and as needed. Withhold fluorouracil until Grade 4 myelosuppression resolves; resume fluorouracil at a reduced dose when myelosuppression has resolved or improved to Grade 1 in severity.

5.8 Mucositis

Mucositis, stomatitis or esophagopharyngitis, which may lead to mucosal sloughing orulceration, can occur with fluorouracil. The incidence is reported to be higher with administration of fluorouracil by intravenous bolus compared with administration by continuous infusion. Withhold fluorouracil administration for Grade 3 or 4 mucositis; resume fluorouracil at a reduced dose once mucositis has resolved or decreased in severity to Grade 1.

5.9 Increased Risk of Elevated International Normalized Ratio (INR) with Warfarin

Clinically significant elevations in coagulation parameters have been reported during concomitant use of warfarin and fluorouracil. Closely monitor patients receiving concomitant coumarin-derivative anticoagulants such as warfarin for INR or prothrombin time in order to adjust the anticoagulant dose accordingly [see Drug Interactions (7)].

5.10 Embryofetal Toxicity

Based on its mechanism of action, fluorouracil can cause fetal harm when administered to a pregnant woman. In animal studies, administration of fluorouracil at doses lower than a human dose of 12 mg/kg caused teratogenicity. If this drug is used during pregnancy, or if the patient becomes pregnant while taking this drug, the patient should be apprised of the potential hazard to a fetus. Advise females of reproductive potential and males with female partners of reproductive potential to use effective contraception during and for 3 months following cessation of therapy with fluorouracil [see Use in Specific Populations (8.1, 8.6), Clinical Pharmacology (12.1), and Nonclinical Toxicology (13.1)].

6 ADVERSE REACTIONS

The following adverse reactions are discussed in more detail in other sections of the labeling:

• Serious Adverse Reactions or Death from Dihydropyrimidine Dehydrogenase (DPD) Deficiency [see Warnings and Precautions (5.1)]
• Cardiotoxicity [see Warnings and Precautions (5.2)]
• Hyperammonemic Encephalopathy [see Warnings and Precautions (5.3)]
• Neurologic Toxicity [see Warnings and Precautions (5.4)]
• Diarrhea [see Warnings and Precautions (5.5)]
• Palmar-Plantar Erythrodysesthesia (Hand-Foot Syndrome) [see Warnings and Precautions (5.6)]
• Myelosuppression [see Warnings and Precautions (5.7) ]
• Mucositis [see Warnings and Precautions (5.8)]
• Increased risk of elevated INR when administrated with warfarin [see Warnings and Precautions (5.9)]

6.2 Postmarketing Experience

The following adverse reactions have been identified during postapproval use of fluorouracil. Because these reactions are reported voluntarily from a population of uncertain size, it is not always possible to reliably estimate their frequency or establish a causal relationship to drug exposure.

Hematologic: pancytopenia [see Warnings and Precautions (5.7)]

Gastrointestinal: gastrointestinal ulceration, nausea, vomiting

Allergic Reactions: anaphylaxis and generalized allergic reactions

Neurologic: nystagmus, headache

Dermatologic: dry skin; fissuring; photosensitivity, as manifested by erythema or increased

pigmentation of the skin; vein pigmentation

Ophthalmic: lacrimal duct stenosis, visual changes, lacrimation, photophobia

Psychiatric: euphoria

Miscellaneous: thrombophlebitis, epistaxis, nail changes (including loss of nails)

7 DRUG INTERACTIONS

7.1 Anticoagulants and CYP 2C9 Substrates

Elevated coagulation times have been reported in patients taking fluorouracil concomitantly with warfarin. While pharmacokinetic data are not available to assess the effect of fluorouracil administration on warfarin pharmacokinetics, the elevation of coagulation times that occurs with the fluorouracil prodrug capecitabine is accompanied by an increase in warfarin concentrations. Thus, the interaction may be due to inhibition of cytochrome P450 2C9 by fluorouracil or its metabolites.

8 USE IN SPECIFIC POPULATIONS

8.1 Pregnancy

Pregnancy Category D

Risk Summary
There are no adequate and well-controlled studies with fluorouracil in pregnant women. Based on its mechanism of action, fluorouracil can cause fetal harm when administered to a pregnant woman. Administration of fluorouracil to rats and mice during selected periods of organogenesis, at doses lower than a human dose of 12 mg/kg, caused embryolethality and teratogenicity. Malformations included cleft palate and skeletal defects. In monkeys, maternal doses of fluorouracil higher than an approximate human dose of 12 mg/kg resulted in abortion. If this drug is used during pregnancy, or if the patient becomes pregnant while taking this drug, apprise the patient of the potential hazard to a fetus [see Clinical Pharmacology (12.1)].

Animal Data
Malformations including cleft palate, skeletal defects and deformed appendages (paws and tails) were observed when fluorouracil was administered by intraperitoneal injection to mice at doses at or above 10 mg/kg (approximately 0.06 times a human dose of 12 mg/kg on a mg/m2 basis) for 4 days during the period of organogenesis. Similar results were observed in hamsters administered fluorouracil intramuscularly at doses lower than those administered in commonly used clinical treatment regimens. In rats, administration of fluorouracil by intraperitoneal injection at doses greater than 15 mg/kg (approximately 0.2 times a human dose of 12 mg/kg on a mg/m2 basis) for a single day during organogenesis resulted in delays in growth and malformations including microanophthalmos. In monkeys, administration of fluorouracil during organogenesis at doses approximately equal to a human dose of 12 mg/kg on a mg/m2 basis resulted in abortion; at a 50% lower dose, resorptions and decreased fetal body weights were reported.

8.3 Nursing Mothers

It is not known whether fluorouracil or its metabolites are present in human milk. Because many drugs are present in human milk and because of the potential for serious adverse reactions in nursing infants from fluorouracil, a decision should be made whether to discontinue nursing or to discontinue the drug, taking into account the importance of the drug to the mother.

8.4 Pediatric Use

The safety and effectiveness in pediatric patients have not been established.

8.5 Geriatric Use

Reported clinical experience has not identified differences in safety or effectiveness between the elderly and younger patients.

8.6 Females and Males of Reproductive Potential

Contraception

Females

Based on its mechanism of action, fluorouracil can cause fetal harm when administered to a pregnant woman. Advise females of reproductive potential to use effective contraception during treatment with fluorouracil and for up to 3 months following cessation of therapy [see Use in Specific Populations (8.1)].

Males

Fluorouracil may damage spermatozoa. Advise males with female partners of reproductive potential to use effective contraception during and for 3 months following cessation of therapy with fluorouracil [see Nonclinical Toxicology (13.1)].

Infertility

Females

Advise females of reproductive potential that, based on animal data, fertility may be impaired while receiving fluorouracil [see Nonclinical Toxicology (13.1)].

Males

Advise males of reproductive potential that, based on animal data, fertility may be impaired while receiving fluorouracil [see Nonclinical Toxicology (13.1)].

10 OVERDOSAGE

Administer uridine triacetate within 96 hours following the end of fluorouracil infusion for management of fluorouracil overdose.

11 DESCRIPTION

Fluorouracil injection USP, a nucleoside metabolic inhibitor, is a colorless to faint yellow, aqueous, sterile, nonpyrogenic injectable solution available in 50 mL and 100 mL pharmacy bulk package, a sterile preparation that contains doses for multiple patients for intravenous administration. Each mL contains 50 mg fluorouracil in water for injection, USP. The pH is adjusted to approximately 9.2 with sodium hydroxide. Chemically, fluorouracil, a fluorinated pyrimidine, is 5-fluoro-2,4 (1H,3H)-pyrimidinedione. Its structural formula is:

Molecular formula: C4H3FN2O2
Molecular weight : 130.08 g/mole

12 CLINICAL PHARMACOLOGY

12.1 Mechanism of Action

Fluorouracil is a nucleoside metabolic inhibitor that interferes with the synthesis of deoxyribonucleic acid (DNA) and to a lesser extent inhibits the formation of ribonucleic acid (RNA); these affect rapidly growing cells and may lead to cell death. Fluorouracil is converted to three main active metabolites: 5-fluoro-2′-deoxyuridine-5′-monophosphate (FdUMP), 5-fluorouridine-5′triphosphate (FUTP) and 5-fluoro-2′-deoxyuridine-5′-triphosphate (FdUTP). These metabolites have several effects including the inhibition of thymidylate synthase by FdUMP, incorporation of FUTP into RNA and incorporation of FdUTP into DNA.

12.3 Pharmacokinetics

Distribution
Following bolus intravenous injection, fluorouracil distributes throughout the body including the intestinal mucosa, bone marrow, liver, cerebrospinal fluid and brain tissue.

Elimination
Following bolus intravenous injection, 5 – 20 % of the parent drug is excreted unchanged in the urine in six hours. The remaining percentage of the administered dose is metabolized, primarily in the liver. The metabolites of fluorouracil (e.g., urea and α-fluoro-ßalanine) are excreted in the urine over 3 to 4 hours.

Following bolus intravenous injection of fluorouracil, as a single agent, the elimination half-life increased with dose from 8 to 20 minutes.

12.5 Pharmacogenomics

The DPYD gene encodes the enzyme DPD, which is responsible for the catabolism of >80% of fluorouracil. Approximately 3-5% of White populations have partial DPD deficiency and 0.2% of White populations have complete DPD deficiency, which may be due to certain genetic no function or decreased function variants in DPYD resulting in partial to complete or near complete absence of enzyme activity. DPD deficiency is estimated to be more prevalent in Black or African American populations compared to White populations. Insufficient information is available to estimate the prevalence of DPD deficiency in other populations.

Patients who are homozygous or compound heterozygous for no function DPYD variants (i.e., carry two no function DPYD variants that result in no DPD enzyme activity) or are compound heterozygous for a no function DPYD variant plus a decreased function DPYD variant have complete DPD deficiency and are at increased risk for acute early-onset of toxicity and serious life-threatening, or fatal adverse reactions due to increased systemic exposure to fluorouracil. Partial DPD deficiency can result from the presence of either two decreased function DPYD variants or one normal function plus either a decreased function or a no function DPYD variant. Patients with partial DPD deficiency may also be at an increased risk for toxicity from fluorouracil.

Several DPYD variants observed with variable frequency across populations have been associated with reduced or no DPD activity, especially when present as homozygous or compound heterozygous variants. These include c.1905+1G>A (DPYD *2A), c.1679T>G (DPYD *13), c.2846A>T, c.1129-5923C>G (Haplotype B3), and c557A>G. DPYD*2A and DPYD*13 are no function variants, and c.2846A>T, c.1129- 5923C>G, and c557A>G are decreased function variants. This is not a complete listing of all DPYD variants that may result in DPD deficiency [see Warnings and Precautions (5.1)].

13 NONCLINICAL TOXICOLOGY

13.1 Carcinogenesis & Mutagenesis & Impairment Of Fertility

Carcinogenicity studies have not been performed with fluorouracil. Fluorouracil was mutagenic in vitro in the bacterial reverse mutation (Ames) assay and induced chromosomal aberrations in hamster fibroblasts in vitro and in mouse bone marrow in the in vivo mouse micronucleus assay.

Administration of fluorouracil intraperitoneally to male rats at dose levels equal to or greater than 1.7-fold the human dose of 12 mg/kg induced chromosomal aberrations in spermatogonia and inhibition of spermatogonia differentiation resulting in transient infertility. In female rats, intraperitoneal administration of fluorouracil during the pre-ovulatory phases of oogenesis at dose levels equal to or greater than 0.33 times a human dose of 12 mg/kg resulted in decreased incidence of fertile matings, increased pre-implantation loss, and fetotoxicity.

15 REFERENCES

"OSHA Hazardous Drugs." OSHA. http://www.osha.gov/SLTC/hazardousdrugs/index.html

16 HOW SUPPLIED/STORAGE AND HANDLING

16.1 How Supplied

Fluorouracil injection USP is supplied in a pharmacy bulk package available in a box containing one vial, as listed below:

• NDC 68001-525-27: one box with one vial, containing 2.5 g/50 mL (50 mg/mL) fluorouracil

• NDC 68001-525-32: one box with one vial, containing 5 g/100 mL (50 mg/mL) fluorouracil

16.2 Storage

Store at 20°C to 25°C (68°F to 77°F). Excursions are permitted from 15°C to 30°C (59°F to 86°F) [see USP Controlled Room Temperature]. Protect from light. Retain in carton until time of use. Fluorouracil is a cytotoxic drug. Follow applicable special handling and disposable procedures [see References (15)].

17 PATIENT COUNSELING INFORMATION

Advise:
• Prior to initiating fluorouracil treatment, inform patients of the potential for serious or fatal adverse reactions due to DPD deficiency and testing for genetic variants of DPYD. Advise patients to immediately contact their healthcare provider if symptoms of severe mucositis, diarrhea, neutropenia, and neurotoxicity occur [see Warnings and Precautions (5.1) and Clinical Pharmacology (12.5)].
• Patients of the risk of cardiotoxicity. Advise patients to immediately contact their healthcare provider or to go to an emergency room for new onset of chest pain, shortness of breath, dizziness, or lightheadedness [see Warnings and Precautions (5.2)].
• Patients to immediately contact their healthcare provider or go to an emergency room for new onset of confusion, disorientation, or otherwise altered mental status; difficulty with balance or coordination; or visual disturbances [see Warnings and Precautions (5.3, 5.4)].
• Patients to contact their healthcare provider for severe diarrhea or for painful mouth sores with decreased oral intake of food or fluids [see Warnings and Precautions (5.5, 5.8)].
• Patients to contact their healthcare provider for tingling or burning, redness, flaking, swelling, blisters, or sores on the palms of their hands or soles of their feet [see Warnings and Precautions (5.6)].
• Patients of the importance of keeping appointments for blood tests. Instruct patients to monitor their temperature on a daily basis and to immediately contact their healthcare provider for fever or other signs of infection [see Warnings and Precautions (5.7)].
• Patients to notify their healthcare provider of all drugs they are taking, including warfarin or other coumarin-derivative anticoagulants. Advise patients of the importance of keeping appointments for blood tests [see Warnings and Precautions (5.9)] .
• Females of reproductive potential and males with female partners of reproductive potential to use effective contraception during treatment with fluorouracil and for up to 3 months after the last dose of fluorouracil. Instruct female patients to contact their healthcare provider if they become pregnant, if pregnancy occurs during fluorouracil treatment or during the 3 months following the last dose [see Warnings and Precautions (5.10), Use in Specific Populations (8.1and 8.6), and Nonclinical Toxicology (13.1)].
• Females and males of reproductive potential may have impaired fertility while receiving fluorouracil, based on animal data [see Use in Specific Populations (8.6) and Nonclinical Toxicology (13.1)].
• Nursing mothers to discontinue nursing [see Use in Specific Populations (8.3)].

Manufactured by:

Gland Pharma Limited
Visakhapatnam – 530049

Unit-II, Block-C,

Phase-1, VSEZ, Duvvada

Andhra Pradesh

India.

For BluePoint Laboratories

Revised: 01/2026

PACKAGE LABEL.PRINCIPAL DISPLAY PANEL

Fluorouracil Injection, USP
NDC 68001-525-27
Vial label-50mL

Carton label-50mL

Fluorouracil Injection, USP
NDC 68001-525-32
Vial label-100mL

Carton label-100mL